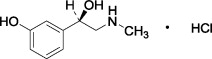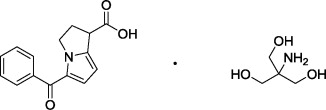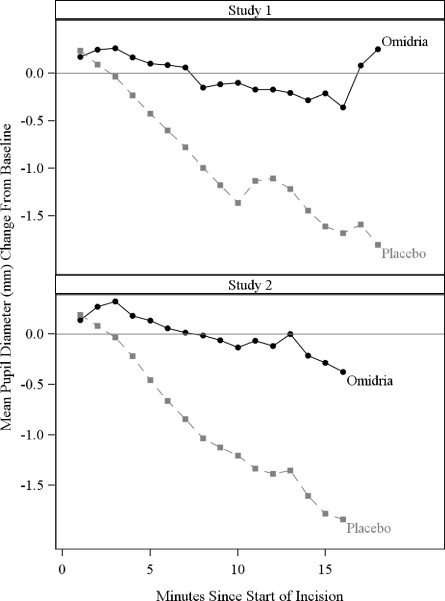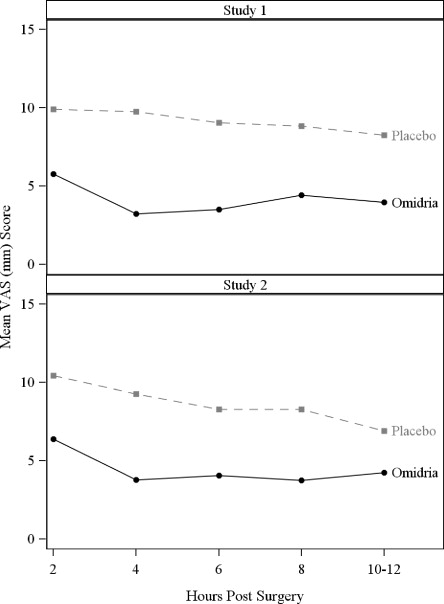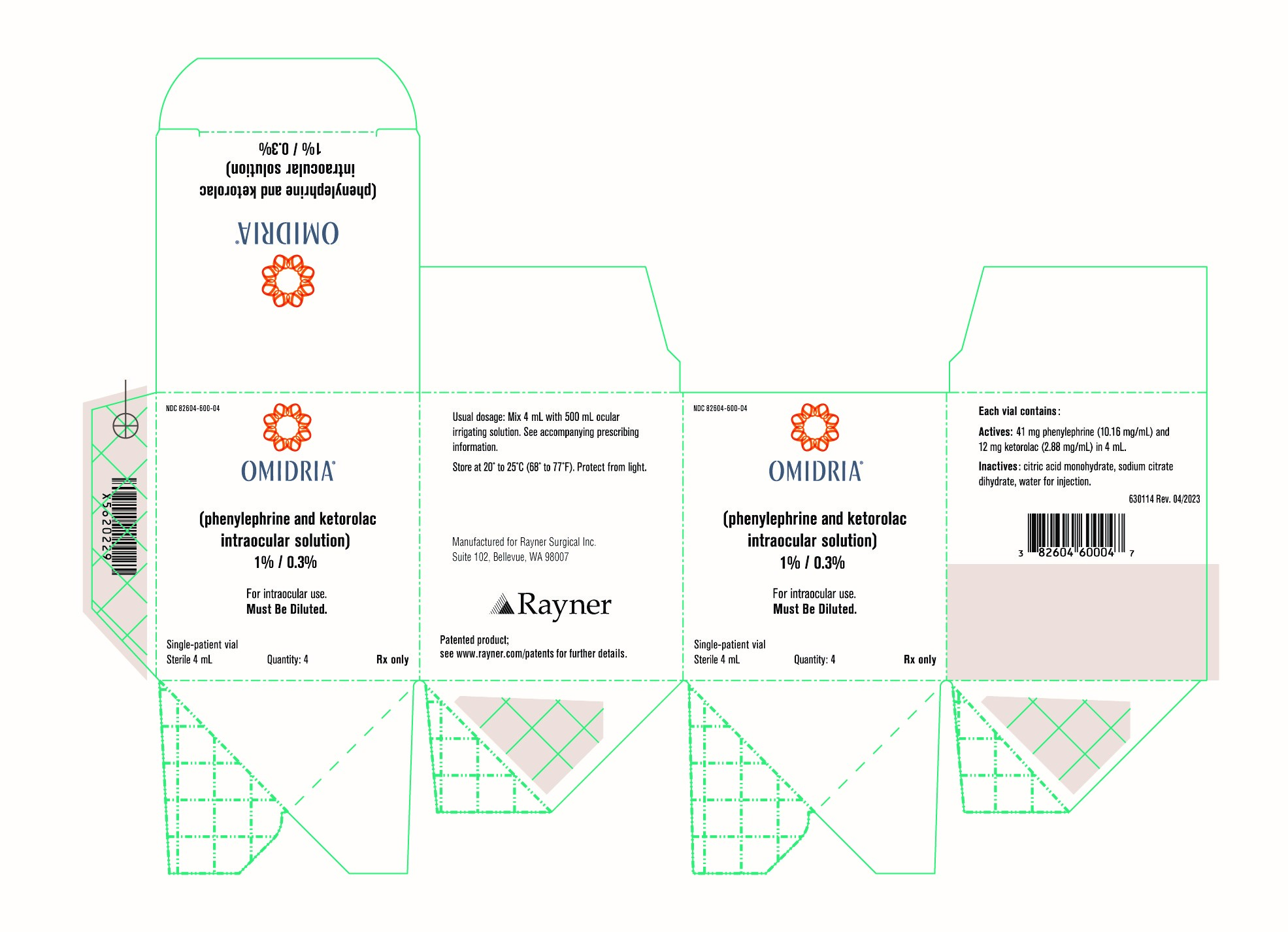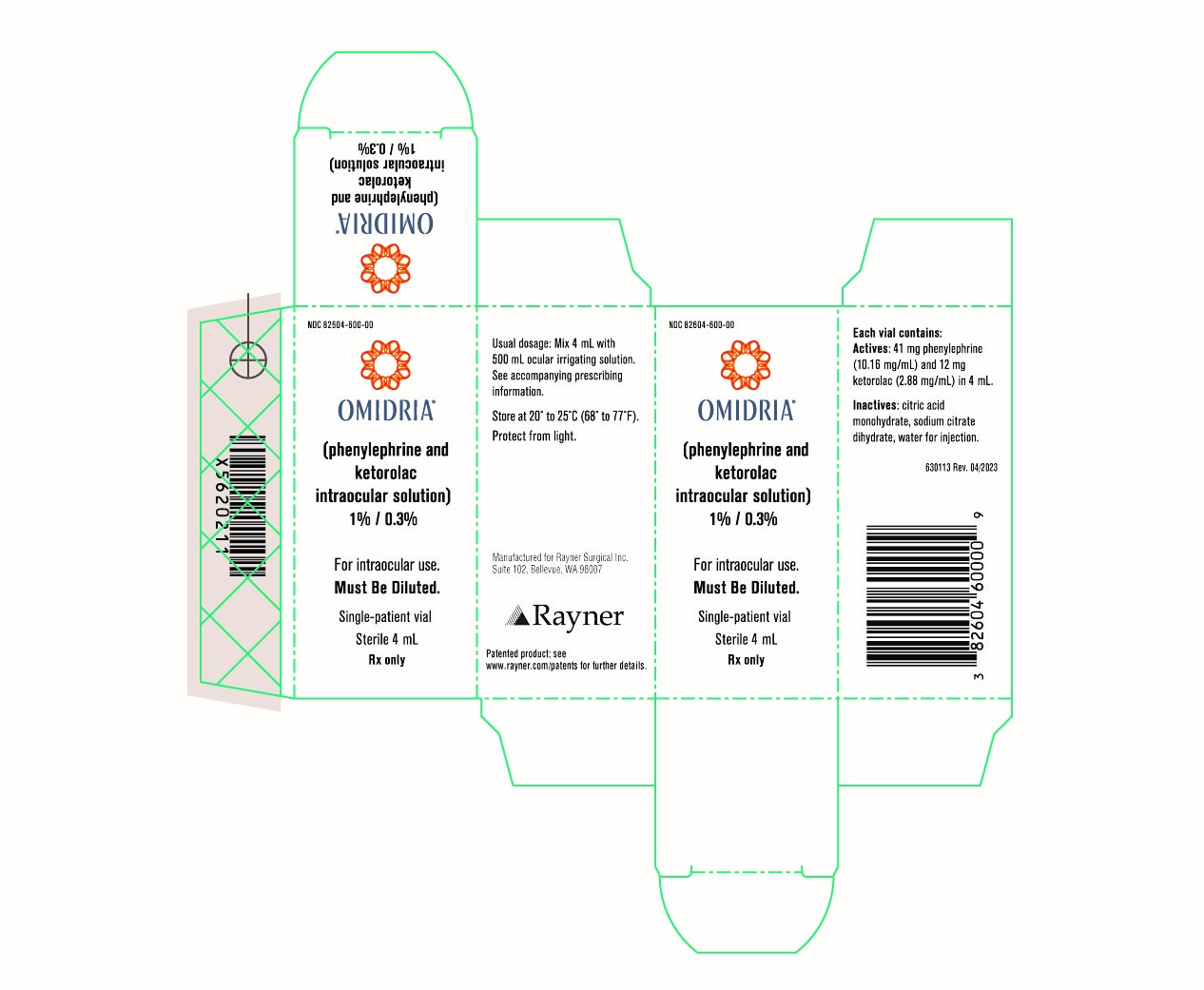 DRUG LABEL: Omidria
NDC: 82604-600 | Form: INJECTION, SOLUTION, CONCENTRATE
Manufacturer: Rayner Surgical Inc.
Category: prescription | Type: HUMAN PRESCRIPTION DRUG LABEL
Date: 20230707

ACTIVE INGREDIENTS: PHENYLEPHRINE
 10.16 mg/1 mL; KETOROLAC
 2.88 mg/1 mL
INACTIVE INGREDIENTS: TRISODIUM CITRATE DIHYDRATE; WATER; CITRIC ACID MONOHYDRATE

HIGHLIGHTS OF PRESCRIBING INFORMATION

These highlights do not include all the information needed to use OMIDRIA® safely and effectively. See full prescribing information for OMIDRIA.
OMIDRIA® (phenylephrine and ketorolac intraocular solution) 1% / 0.3%, for addition to ocular irrigating solution
Initial U.S. Approval: 2014

1 INDICATIONS AND USAGE

OMIDRIA is an alpha 1-adrenergic receptor agonist and nonselective cyclooxygenase inhibitor indicated for:

- Maintaining pupil size by preventing intraoperative miosis (1)
- Reducing postoperative pain (1)

OMIDRIA is added to an ocular irrigating solution used during cataract surgery or intraocular lens replacement.

2 DOSAGE AND ADMINISTRATION

- Each vial of OMIDRIA must be diluted prior to use for administration to a single patient undergoing cataract surgery or intraocular lens replacement.
- Dilute 4 mL of OMIDRIA in 500 mL of ocular irrigating solution. Irrigation solution is to be used as needed for the surgical procedure. (2)

3 DOSAGE FORMS AND STRENGTHS

Intraocular solution containing phenylephrine 10.16 mg/mL (1%) and ketorolac 2.88 mg/mL (0.3%) for use in a single patient. (3)

4 CONTRAINDICATIONS

Hypersensitivity to any component of this product (4)

5 WARNINGS AND PRECAUTIONS

Systemic exposure to phenylephrine can cause elevations in blood pressure (5.1).

6 ADVERSE REACTIONS

The most common reported adverse reactions (≥2%) are eye irritation, posterior capsule opacification, increased intraocular pressure, and anterior chamber inflammation. (6.1)

To report SUSPECTED ADVERSE REACTIONS, contact Rayner Surgical Inc. at 1-877-0MIDRIA or FDA at 1-800-FDA-1088 or www.fda.gov/medwatch.

FULL PRESCRIBING INFORMATION

1 INDICATIONS AND USAGE

Omidria® is added to an ocular irrigating solution used during cataract surgery or intraocular lens replacement and is indicated for maintaining pupil size by preventing intraoperative miosis and reducing postoperative ocular pain.

2 DOSAGE AND ADMINISTRATION

Omidria must be diluted prior to intraocular use. For administration to patients undergoing cataract surgery or intraocular lens replacement, 4 mL of Omidria is diluted in 500 mL of ocular irrigating solution. Irrigation solution is to be used as needed for the surgical procedure for a single patient.

The storage period for the diluted product is not more than 4 hours at room temperature or 24 hours under refrigerated conditions.

Do not use if the solution is cloudy or if it contains particulate matter.

3 DOSAGE FORMS AND STRENGTHS

Omidria is an intraocular solution containing 10.16 mg/mL (1% w/v) of phenylephrine and 2.88 mg/mL (0.3% w/v) of ketorolac for use in a single patient.

4 CONTRAINDICATIONS

Omidria is contraindicated in patients with a known hypersensitivity to any of its ingredients.

5 WARNINGS AND PRECAUTIONS

5.1 Elevated Blood Pressure

Systemic exposure to phenylephrine can cause elevations in blood pressure.

5.2 Cross-Sensitivity or Hypersensitivity

There is the potential for cross-sensitivity to acetylsalicylic acid, phenylacetic acid derivatives, and other non-steroidal anti- inflammatory drugs (NSAIDs). There have been reports of bronchospasm or exacerbation of asthma associated with the use of ketorolac in patien ts who either have a known hypersensitivity to aspirin/NSAIDs or a past medical history of asthma. Therefore, use Omidria with caution in individuals who have previously exhibited sensitivities to these drugs.

6 ADVERSE REACTIONS

6.1 Clinical Studies Experience

Because clinical studies are conducted under widely varying conditions, adverse reaction rates observed in the clinical studies of a drug cannot be directly compared to the rates in the clinical studies of another drug and may not reflect the rates observed in practice.

Table 1 shows frequently reported ocular adverse reactions with an incidence of ≥ 2% of adult patients as seen in the combined clinical trial results from three randomized, placebo-controlled studies [see Clinical Studies (14)] .

Table 1: Ocular Adverse Reactions Reported by ≥ 2% of Adult Patients
MedDRA Preferred Term | Placebo (N=462) | Omidria (N=459)
 | n (%) | n (%)
Ocular Events
Anterior Chamber Inflammation | 102 (22%) | 111 (24%)
Intraocular Pressure Increased | 15 (3%) | 20 (4%)
Posterior Capsule Opacification | 16 (4%) | 18 (4%)
Eye Irritation | 6 (1%) | 9 (2%)
Foreign Body Sensation in Eyes | 11 (2%) | 8 (2%)

In a safety study that enrolled 72 pediatric patients up to 3 years old, no overall difference in safety was observed between pediatric and adult patients.

8 USE IN SPECIFIC POPULATIONS

8.1 Pregnancy

Risk Summary
There are no available data on Omidria use in pregnant women or animals to inform
any drug-associated risks. Oral administration of ketorolac to rats during late
gestation produced dystocia and increased pup mortality at a dose 740-times the
plasma exposure at the recommended human ophthalmic dose (RHOD). Since
human systemic exposure to Omidria following a lens replacement procedure is low
(see Clinical Pharmacology (12.3)], the applicability of animal findings to the risk
of Omidria in humans during pregnancy is unclear. Omidria should be used during
pregnancy only if the potential benefit justifies the potential risk to the fetus.
Clinical Considerations
Fetal/Neonatal Adverse Reactions
Premature closure of the ductus arteriosus in the fetus has occurred with third
trimester use of oral and injectable NSAIDs. Ketorolac plasma concentrations are
detectable following ocular Omidria administration [see Clinical Pharmacology (12.3)].
The use of Omidria during late pregnancy should be avoided.
.Q.a1a
Animal Data
No well-controlled animal reproduction studies have been conducted with Omidria
or phenylephrine.
Ketorolac, administered during organogenesis, did not cause embryofetal abnormalities
or mortalities in rabbits or rats at oral doses of 3.6 mg/kg/day and 10 mg/kg/day,
respectively. These doses produced systemic exposure that is 1150 times and
4960 times the plasma exposure (based on Cma,c) at the RHOD, respectively. When
administered to rats during late gestation (after Day 17 of gestation) at oral doses
up to 1.5 mg/kg/day (740 times the plasma exposure at the RHOD), ketorolac
produced dystocia and increased pup mortality.

Risk Summary

There are no available data on Omidria use in pregnant women or animals to inform any drug-associated risks. Oral administration of ketorolac to rats during late gestation produced dystocia and increased pup mortality at a dose 740-times the plasma exposure at the recommended human ophthalmic dose (RHOD). Since human systemic exposure to Omidria following a lens replacement procedure is low [ see Clinical Pharmacology (12.3) ], the applicability of animal findings to the risk of Omidria in humans during pregnancy is unclear. Omidria should be used during pregnancy only if the potential benefit justifies the potential risk to the fetus.

Clinical Considerations

Fetal/Neonatal Adverse Reactions

Premature closure of the ductus arteriosus in the fetus has occurred with third trimester use of oral and injectable NSAIDs. Ketorolac plasma concentrations are detectable following ocular Omidria administration [see Clinical Pharmacology (12.3)] . The use of Omidria during late pregnancy should be avoided.

Data

Animal Data

No well-controlled animal reproduction studies have been conducted with Omidria or phenylephrine.

Ketorolac, administered during organogenesis, did not cause embryofetal abnormalities or mortalities in rabbits or rats at oral doses of 3.6 mg/kg/day and 10 mg/kg/day, respectively. These doses produced systemic exposure that is 1150 times and 4960 times the plasma exposure (based on Cmax) at the RHOD, respectively. When administered to rats during late gestation (after Day 17 of gestation) at oral doses up to 1.5 mg/kg/day (740 times the plasma exposure at the RHOD) , ketorolac produced dystocia and increased pup mortality.

8.2 Lactation

Risk Summary

There are no data on the presence of Omidria in human milk, the effects on the breastfed infant, or the effects on milk production. Howerver, systemic exposure to Omidria, following a lens replacement procedure is low [see Clinical Pharmacology (12.3)] . The developmental and health benefits of breastfeeding should be considered along with the mother's clinical need for Omidria and any potential adverse effects on the breastfed child from Omidria.

8.4 Pediatric Use

The safety and effectiveness of Omidria have been established in the pediatric population from neonates to adolescents (birth to younger than 17 years). Use of Omidria in this population is supported by evidence from adequate and well-controlled studies of Omidria in adults with additional data from a single active-controlled safety study in pediatric patients up to 3 years old [see Clinical Studies (14)] .

No overall differences in safety were observed between pediatric and adult patients.

8.5 Geriatric Use

No overall differences in safety or effectiveness have been observed between elderly and adult patients.

10 OVERDOSAGE

Systemic overdosage of phenylephrine may cause a rise in blood pressure. It may also cause headache, anxiety, nausea, vomiting, and ventricular arrhythmias. Supportive care is recommended.

11 DESCRIPTION

Omidria is a sterile aqueous solution, containing the α1-adrenergic receptor agonist phenylephrine HCl and the nonsteroidal anti-inflammatory ketorolac tromethamine, for addition to ocular irrigating solution.

The descriptions and structural formulae are:

Phenylephrine Hydrochloride Drug Substance:

Common Name: | phenylephrine hydrochloride
Chemical Name: | (-)- m-Hydroxy-α-[(methylamino)methyl]benzyl alcohol hydrochloride
Molecular Formula: | C9H13NO2 · HCl
Molecular Weight: | 203.67 g/mole

Figure 1: Chemical Structure for Phenylephrine HCl

Ketorolac Tromethamine Drug Substance:

Common Name: | ketorolac tromethamine
Chemical Name: | (±)-5-Benzoyl-2,3-dihydro-1H-pyrrolizine-1-carboxylic acid : 2-amino-2-(hydroxymethyl)-1,3-propanediol (1:1)
Molecular Formula: | C15H13NO3 · C4H11NO3
Molecular Weight: | 376.40 g/mole

Figure 2: Chemical Structure for Ketorolac Tromethamine

Omidria is a clear, colorless to slightly yellow, sterile solution concentrate with a pH of approximately 6.3.

Each vial of Omidria contains:

Actives: phenylephrine hydrochloride 12.4 mg/mL equivalent to 10.16 mg/mL of phenylephrine and ketorolac tromethamine 4.24 mg/mL equivalent to 2.88 mg/mL of ketorolac.

Inactives: citric acid monohydrate; sodium citrate dihydrate; water for injection; may include sodium hydroxide and/or hydrochloric acid for pH adjustment.

12 CLINICAL PHARMACOLOGY

12.1 Mechanism of Action

The two active pharmaceutical ingredients (API) in Omidria, phenylephrine and ketorolac, act to maintain pupil size by preventing intraoperative miosis, and reducing postoperative pain.

Phenylephrine is an α1-adrenergic receptor agonist and, in the eye, acts as a mydriatic agent by contracting the radial muscle of the iris. Ketorolac is a nonsteroidal anti-inflammatory that inhibits both cyclooxygenase enzymes (COX-1 and COX-2), resulting in a decrease in tissue concentrations of prostaglandins to reduce pain due to surgical trauma. Ketorolac, by inhibiting prostaglandin synthesis secondary to ocular surgical insult or direct mechanical stimulation of the iris, also prevents surgically induced miosis.

12.3 Pharmacokinetics

In a pharmacokinetic study evaluating Omidria, systemic exposure to both phenylephrine and ketorolac was low or undetectable.

A single-dose of Omidria as part of the irrigation solution was administered in 14 patients during lens replacement surgery. The volume of irrigation solution used during surgery ranged between 150 mL to 300 mL (median 212.5 mL). Detectable phenylephrine plasma concentrations were observed in one of 14 patients (range 1.2 to 1.4 ng/mL) during the first 2 hours after the initiation of Omidria administration. The observed phenylephrine plasma concentrations could not be distinguished from the preoperative administration of phenylephrine 2.5% ophthalmic solution prior to exposure to Omidria.

Ketorolac plasma concentrations were detected in 10 of 14 patients (range 1.0 to 4.2 ng/mL) during the first 8 hours after the initiation of Omidria administration. The maximum ketorolac concentration was 15 ng/mL at 24 hours after the initiation of Omidria administration, which may have been due to application of postoperative ketorolac ophthalmic solution.

14 CLINICAL STUDIES

Studies in Adults

The efficacy and safety of Omidria were evaluated in two Phase 3, randomized, multicenter, double-masked, placebo-controlled clinical trials in 808 adult patients undergoing cataract surgery or intraocular lens replacement.

Patients were randomized to either Omidria or placebo. Patients were treated with preoperative topical mydriatic and anesthetic agents. Pupil diameter was measured throughout the surgical procedure. Postoperative pain was evaluated by self-administered 0-100 mm visual analog scales (VAS).

Mydriasis was maintained in the Omidria-treated groups while the placebo-treated groups experienced progressive constriction.

Figure 3: Intraoperative Pupil Diameter (mm) Change-from-Baseline

At the end of cortical clean-up, 23% of placebo-treated patients and 4% of Omidria-treated patients had a pupil diameter less than 6 mm (p < 0.01).

Pain during the initial 10-12 hours postoperatively was statistically significantly less in the Omidria-treated groups than in the placebo-treated groups.

Figure 4: Postoperative Mean Visual Analog Scale (VAS) Scores for Pain

During the 10-12 hours postoperatively, 26% of Omidria-treated patients reported no pain (VAS = 0 at all timepoints) while 17% of placebo-treated patients reported no pain (p < 0.01).

Study in Pediatric Patients

The safety of Omidria was evaluated in a single, randomized, multicenter, double-masked, active-controlled clinical study in 72 pediatric patients up to 3 years old undergoing cataract surgery with or without intraocular lens replacement.

Patients were randomized to either Omidria or phenylephrine. Patients were treated with preoperative topical mydriatic and anesthetic agents. As in the adult studies, mydriasis was maintained in the Omidria-treated group. No overall differences in safety were observed between pediatric and adult patients.

16 HOW SUPPLIED/STORAGE AND HANDLING

Omidria (phenylephrine and ketorolac intraocular solution) 1%/0.3% is supplied in a clear, 5-mL glass, single-patient-use vial containing 4 mL of sterile solution, for addition to ocular irrigating solution.

Omidria is supplied in a multi-pack containing:

4 vials : NDC 82604-600-04 or

1 vials: NDC 82604-600-00

STORAGE AND HANDLING

Storage: Store at 20˚ to 25˚C (68˚ to 77˚F). Protect from light.

17 PATIENT COUNSELING INFORMATION

Inform patients that they may experience sensitivity to light.

Rayner Surgical Inc.
Suite 102, 14335 NE 24 Street
Bellevue, WA 98007

© Rayner 2023

Patented product; see www.rayner.com/patents for further details.

OMIDRIA®and the OMIDRIA® Logo are registered trademarks of Rayner Surgical Inc.

640069

PRINCIPAL DISPLAY PANEL

NDC 82604-600-04

OMIDRIA®

(phenylephrine and ketorolac intraocular solution)

1% / 0.3%

For Intraocular use.

Must Be Diluted.

Single-Patient vial

Sterile 4 mL

Quantity: 4

Rx Only

NDC 82604-600-00

OMIDRIA ®

(phenylephrine and ketorolac intraocular solution)

1% / 0.3%

For Intraocular use.

Must Be Diluted.

Single-Patient vial

Sterile 4 mL

Quantity: 1

Rx Only